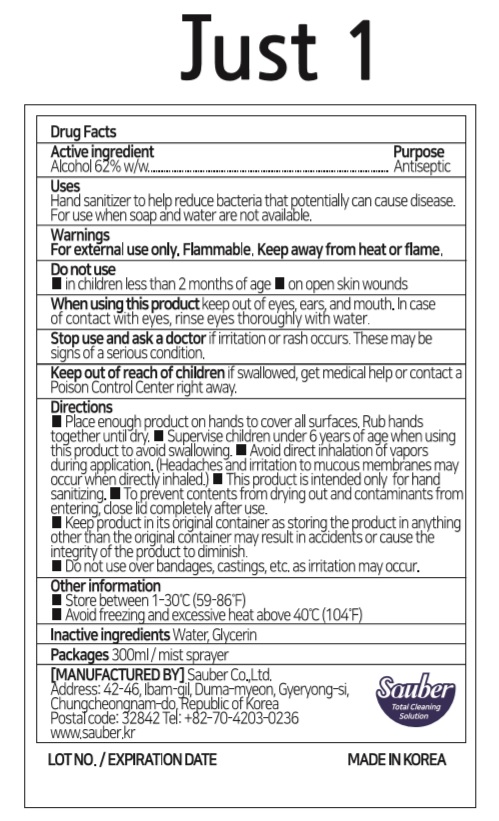 DRUG LABEL: Just 1
NDC: 78880-623 | Form: SPRAY
Manufacturer: Sauber Co.,Ltd.
Category: otc | Type: HUMAN OTC DRUG LABEL
Date: 20200710

ACTIVE INGREDIENTS: ALCOHOL 186 mL/300 mL
INACTIVE INGREDIENTS: GLYCERIN; WATER

Just 1 | 300 ml | Mist sprayer